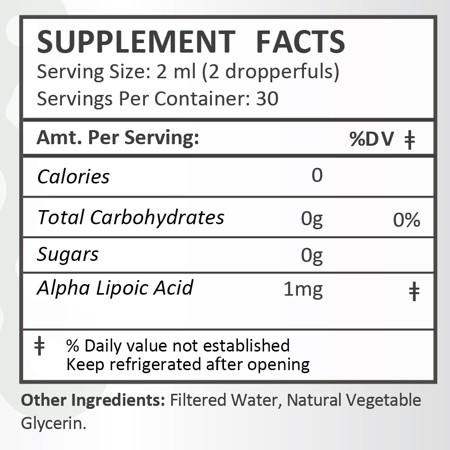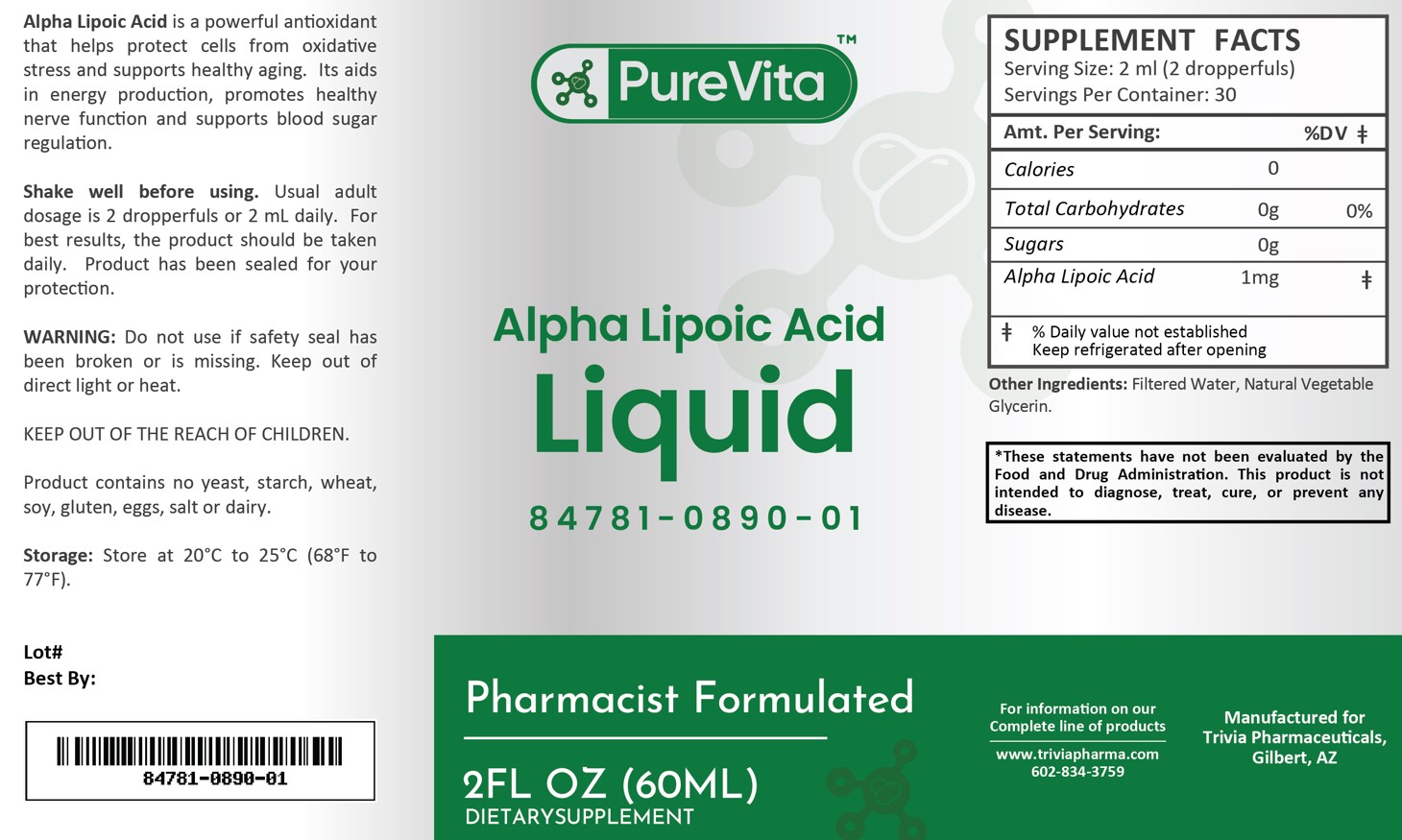 DRUG LABEL: PureVita Alpha Lipoic Acid
NDC: 84781-890 | Form: LIQUID
Manufacturer: Trivia Pharmaceuticals
Category: other | Type: Dietary Supplement
Date: 20250217

ACTIVE INGREDIENTS: ALPHA LIPOIC ACID 1 mg/2 mL

PureVita Alpha Lipoic Acid 1 mg

Health Claim:

PureVita Alpha Lipoic Acid 1 mg

Description:

Pure Vita Alpha Lipoic Acid 1 mg Liquid is a powerful antioxidant that helps product cells from oxidative stress and supports healty aging. It aids in energy products, promotes healthy nerve function and supports blood sugar regulation.

This listed product is not a National Drug Code, but instead has merely been formatted to comply with standard industry practice for pharmacy and insurance computer systems.

Warnings:

Do not use if safety seal has been broken or is missing. Keep out of direct light or heat.

KEEP OUT OF THE REACH OF CHILDREN.

Product contains no yeast, starch, wheat, soy, gluten, eggs, salt or dairy.

Dosage and Adminsitration:

Usual adult dose is 2 dropperfuls or 2 mL daily. For the best results, the product should be taken daily. Product has been sealed for your protection.

How Supplied:

PureVita Alpha Lipoic Acid 1 mg Liquid is supplied as clear, white liquid.

84781-0890-01

Reserved for Professional Recommendation

All prescriptions using this product shall be pursuant to state statutes as applicable. This is not an Orange Book product. There are no implied or explicit claims on therapeutic equivalence.

Manufactured for:
Trivia Pharmaceuticals

Gilbert, AZ

Storage:

Storage: Store at 20^0C to 25^0C (68^0F to 77^0F). Keep refrigerated after opening.